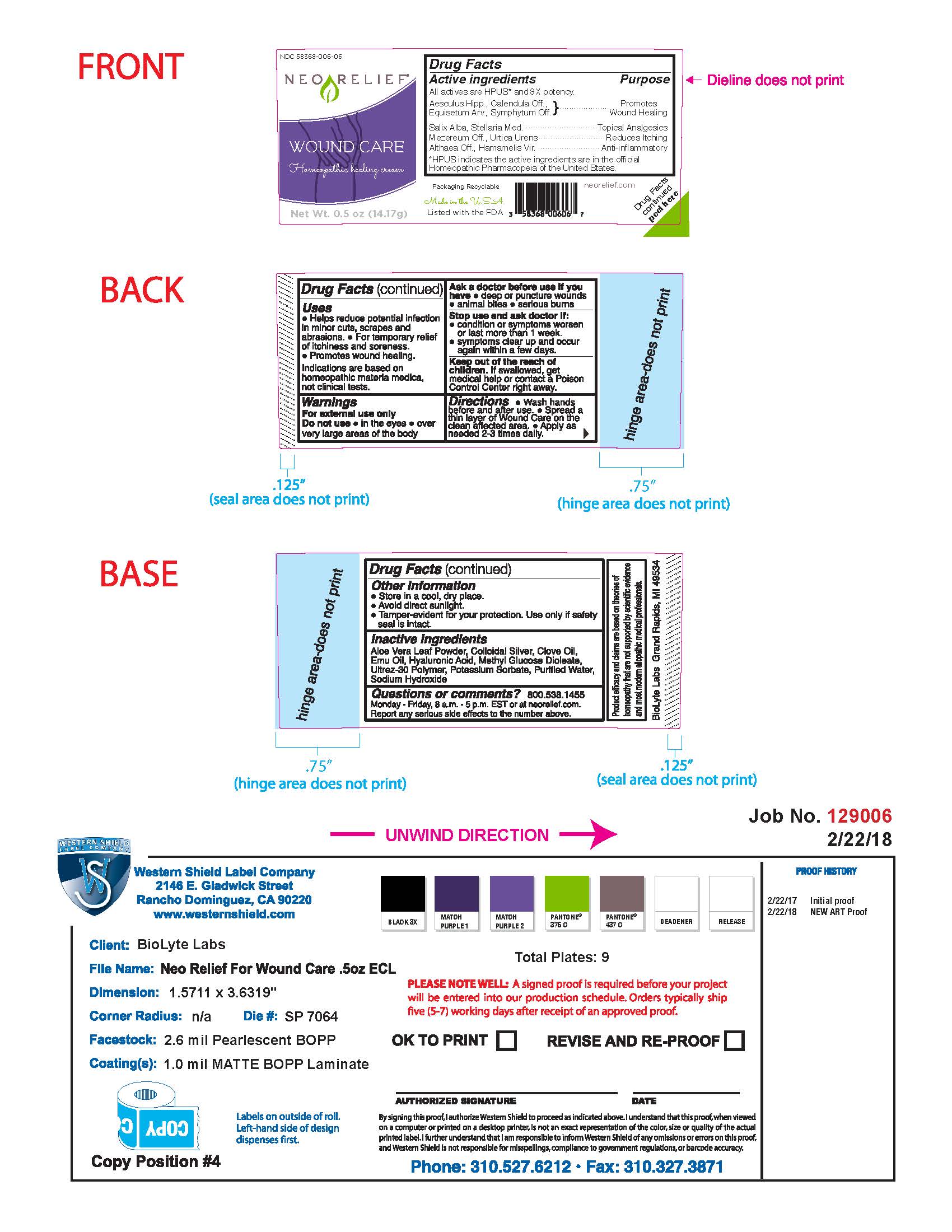 DRUG LABEL: NeoRelief Wound Care
NDC: 58368-006 | Form: CREAM
Manufacturer: BioLyte Laboratories, LLC
Category: homeopathic | Type: HUMAN OTC DRUG LABEL
Date: 20260127

ACTIVE INGREDIENTS: SALIX ALBA BARK 3 [hp_X]/1 g; STELLARIA MEDIA 3 [hp_X]/1 g; DAPHNE MEZEREUM BARK 3 [hp_X]/1 g; URTICA URENS 2 [hp_X]/1 g; ALTHAEA OFFICINALIS ROOT 3 [hp_X]/1 g; HAMAMELIS VIRGINIANA ROOT BARK/STEM BARK 3 [hp_X]/1 g; HORSE CHESTNUT 3 [hp_X]/1 g; CALENDULA OFFICINALIS FLOWERING TOP 3 [hp_X]/1 g; EQUISETUM ARVENSE TOP 3 [hp_X]/1 g
INACTIVE INGREDIENTS: ANHYDROUS CITRIC ACID; METHYL GLUCOSE DIOLEATE; WATER; CARBOMER INTERPOLYMER TYPE A (ALLYL SUCROSE CROSSLINKED); SILVER; ALOE VERA LEAF; CLOVE OIL; EMU OIL; HYALURONIC ACID; POTASSIUM SORBATE; SODIUM HYDROXIDE

Drug Facts Active Ingredients

All actives are HPUS* and 3X potency.

Aesculus Hipp., Calendula Off., Equisetum Arv., Symphytum Off.

Salix Alba, Setllaria Med.

Mezereum Off., Urtica Urens

Althaea Off., Hamamelis Vir.

*HPUS indicates the active ingredients are in the official Homeopathic Pharmacopeia of the United States.

Purpose

Promotes Wound Healing

Topical Analgesics

Reduces Itching

Anti-inflammatory

Uses

Helps reduce potential infection in minor cuts, scrapes and abrasions.

For the temporary relief of itchiness and soreness.

Promotoes wound healing.

Indications are based on homeopathic materia medica, not clinical tests.

Warnings

For external use only.

Do not use in the eyes, over very large areas of the body.

Warnings

Ask a doctor before use if you have deep or puncture wounds, animal bites, serious burns.

Warnings

Stop use and ask doctor if condition or symptoms worsen or last more than 1 week; symptoms clear up and occur again within a few days.

Warnings

Keep out of reach of children. If swallowed, get medical help or contact a Poison Control Center right away.

Directions

Wash hands before and after use; spread a thin layer of Wound Care on the clean affected area; Apply as needed 2-3 times daily.

Other Information

Store in a cool, dry place.

Avoid direct sunlight.

Tamper-evident for your protection. Use only if safety seal is intact.

Inactive Ingredients

Aloe Vera Leaf Powder, Colloidal Silver, Clove Oil, Emu Oil, Hyaluronic Acid, Methyl Glucose Dioleate, Ultrez-30 Polymer, Potassium Sorbate, Purified Water, Sodium Hydroxide

Questions or Comments?

800.538.1455

Monday-Friday, 8 a.m. - 5 p.m. EST or at neorelief.com.

Report any serious side effects to the number above.

Addtional Label Content

Packaging Recyclable

Made in the USA

Listed with the FDA

neorelief.com

Drug Facts peeled here

FTC disclosure: Product efficacy and claims are based on theories of homeopathy that are not supported by scientific evidence and most modern allopathic medical professionals.

BioLyte Labs Grand Rapids, MI 49534

NEO RELIEF WOUND CARE

NDC 58368-006-06

NEO RELIEF

WOUND CARE

Homeopathic healing cream

Net Wt. 0.5 oz (14.17g)